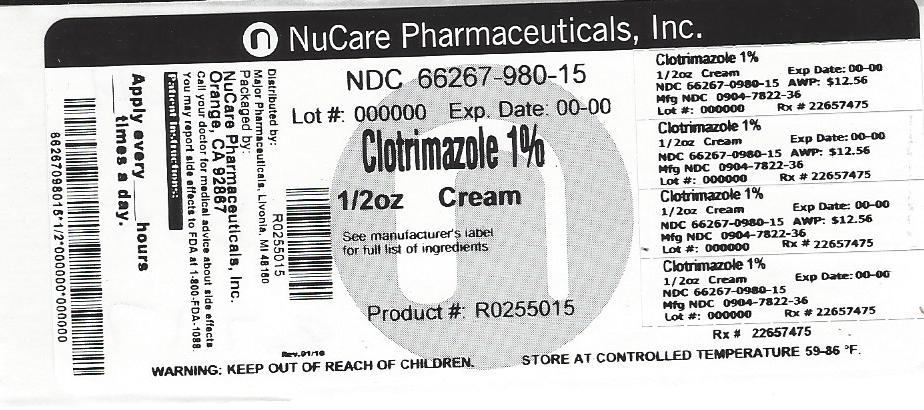 DRUG LABEL: Major Clotrimazole
NDC: 66267-980 | Form: CREAM
Manufacturer: NuCare Pharmaceuticals,Inc.
Category: otc | Type: HUMAN OTC DRUG LABEL
Date: 20240814

ACTIVE INGREDIENTS: CLOTRIMAZOLE 10 mg/1 g
INACTIVE INGREDIENTS: WATER; CETOSTEARYL ALCOHOL; POLYSORBATE 60; BENZYL ALCOHOL; SORBITAN MONOSTEARATE; .ALPHA.-TOCOPHEROL ACETATE; ALOE VERA LEAF; OCTYLDODECANOL; CETYL PALMITATE

Drug Facts

Active ingredient

Clotrimazole USP 1% w/w

Purpose

Antifungal Cream

Uses

Cures athlete's foot (tinea pedis), jock itch (tinea cruris), ringworm (tinea corporis). Relieves the itching, irritation, redness, scaling and discomfort which can accompany these conditions.

Warnings

- Do not use on children under 2 years of age unless directed by a doctor.
- For external use only.
- Avoid contact with eyes.
- If irritation occurs or if there is no improvement within 4 weeks (for athlete's foot or ringworm) or within 2 weeks (for jock itch), discontinue use and consult a doctor.

KEEP OUT OF REACH OF CHILDREN

- Keep this and all drugs out of the reach of children.

In case of accidental ingestion, seek professional assistance or contact a Poison Control Center immediately.

Directions

- Clean the affected area and dry thoroughly.
- Apply a thin layer of this product over affected area twice daily (morning and night), or as directed by a doctor.
- Supervise children in the use of this product.
- For athlete's foot, pay special attention to the spaces between the toes; wear well-fitting ventilated shoes, and change shoes and socks at least once daily.
- For athlete's foot and ringworm, use daily for 4 weeks. For jock itch, use daily for 2 weeks.
- If conditions persists longer, consult a doctor.
- This product is not effective on the scalp or nails.

Other information

- Store at controlled room temperature 15°-30°C (59°-86°F).
- Close cap tightly after use.

Inactive ingredients

aloe vera, benzyl alcohol, cetearyl alcohol, 2-octyldodecanol, polysorbate 60, sorbitan monostearate, spermwax, vitamin E, water

Questions?

Adverse Drug Event call (800)616-2471
Dist. By MAJOR PHARMACEUTICALS
31778 Enterprise Drive, Livonia, Ml 48150 USA
Re-Oder No. 100431